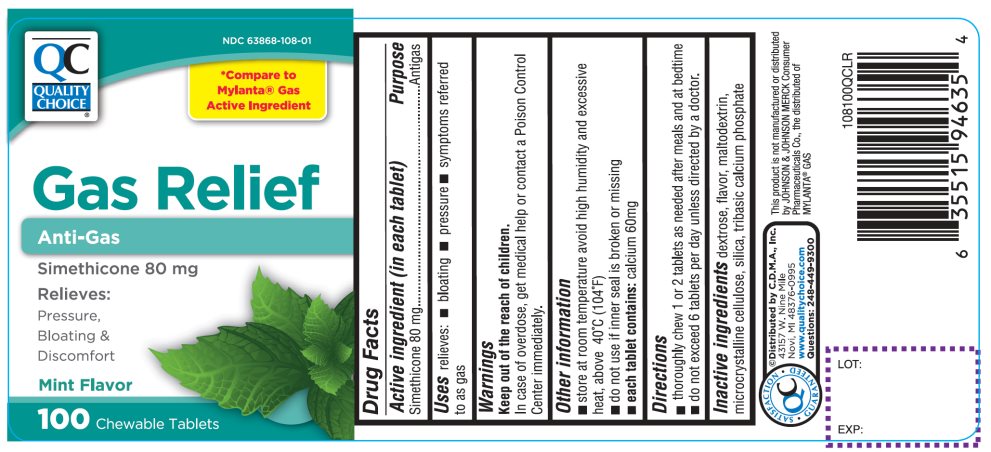 DRUG LABEL: QC Gas Relief

NDC: 63868-108 | Form: TABLET, CHEWABLE
Manufacturer: QUALITY CHOICE (CHAIN DRUG MARKETING ASSOCIATION)
Category: otc | Type: HUMAN OTC DRUG LABEL
Date: 20251203

ACTIVE INGREDIENTS: DIMETHICONE, UNSPECIFIED 80 mg/1 1
INACTIVE INGREDIENTS: DEXTROSE, UNSPECIFIED FORM; PEPPERMINT; MALTODEXTRIN; MICROCRYSTALLINE CELLULOSE; SILICON DIOXIDE; TRICALCIUM PHOSPHATE

Quality Choice Simethicone Gas Relief 100 Chewable Tablets

Active ingredient (in each tablet)

Simethicone 80 mg

Purpose

Antigas

Uses

Relieves:

- bloating
- pressure
- fullness
- stuffed feeling

Directions

- thoroughly chew 1 to 2 tablets as needed after meals and at bedtime
- do not exceed 6 tablets per day unless directed by a doctor

Other information

- store at room temperature avoid high humidity and excessive heat, above 40ºC (104ºF)
- do not use if inner seal is broken or missing
- each tablets contains:calcium 60mg

Inactive ingredients

dextrose, peppermint flavor, maltodextrin, microcrystalline cellulose, silica, tribasic calcium phosphate

Principal Display Panel

NDC 63868-108-01

QUALITY CHOICE®

*Compare to the Mylanta®Gas Active Ingredient

Gas Relief

Anti Gas
Simethicone 80 mg

Relieves:
Pressure

Bloating &

Discomfort

Mint Flavor

100 CHEWABLE TABLETS

QC SATISFACTION GURANTEED

Distributed by C.D.M.A., Inc.

43157 W. Nine Mile

Novi, MI 48376-0995

www.qualitychoice.com

Questions: 248-449-9300

This product is not manufactured or distributed by JOHNSON & JOHNSON MERCK Consumer Pharmaceuticals Co., the distributed of MYLANTA®GAS